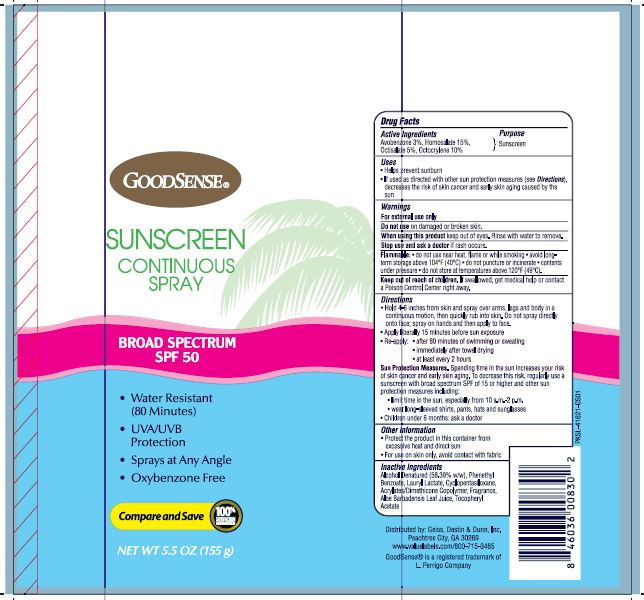 DRUG LABEL: GoodSense SPF 50 CSpray
NDC: 70281-634 | Form: SPRAY
Manufacturer: Solskyn Personal Care LLC
Category: otc | Type: HUMAN OTC DRUG LABEL
Date: 20190807

ACTIVE INGREDIENTS: OCTOCRYLENE 10 g/100 g; AVOBENZONE 3 g/100 g; OCTISALATE 5 g/100 g; HOMOSALATE 15 g/100 g
INACTIVE INGREDIENTS: ALCOHOL; LAURYL LACTATE; .ALPHA.-TOCOPHEROL ACETATE; ALOE VERA LEAF; PHENETHYL BENZOATE; DIMETHICONE CROSSPOLYMER (450000 MPA.S AT 12% IN CYCLOPENTASILOXANE)

GoodSense SPF 50 CSpray TC (Trimline Can)

Active Ingredients

Avobenzone 3%

Homosalate 15%

Octisalate 5%

Octocrylene 10%

Purpose

Sunscreen

Uses

- Helps prevent sunburn.
- If used as directed with other sun protection measures (see Directions), decreases the risk of skin cancer and early skin aging caused by the sun

Warnings

For external use only

Do not use on damaged or broken skin.

When using this product keep out of eyes. Rinse with water to remove.

Stop use and ask a doctor if rash occurs.

Flammable

Flammable: ● do not use near heat, flame or while smoking ● avoid long –term storage above 104oF(40oC) ● do not puncture or incinerate ● contents under pressure ● do not store at temperature above 120oF(49oC).

Keep out of reach of children. If swallowed, get medical help or contact a Poison Control Center right away.

Directions

- Hold 4-6 inches from skin and spray over arms, legs, and body in a continuous motion, then quickly rub into skin. Do not spray directly onto face; spray on hands and then apply to face.
- Apply liberally 15 minutes before sun exposure
- Re-apply:
  - after 80- minutes of swimming or sweating
  - Immediately after towel drying
  - At least every 2 hours

Sun Protection Measures. Spending time in the sun increases your risk of skin cancer and early skin aging. To decrease this risk, regularly use a sunscreen with broad-spectrum SPF of 15 or high and other sun protection measures including:

- Limit time in the sun, especially from 10a.m.-2 p.m.
- Wear long-sleeved shirts, pants, hats, and sunglasses.

- Children under 6 months: Ask a doctor

Other Information

- Protect the product in this container from excessive heat and direct sun
- For use on skin only, avoid contact with fabric

Questions

Distributed by:

Geiss, Destin & Dunn, Inc.

Peach tree City, GA 30269

www.valuelabels.com

800-715-3485

GoodSense® is a registered trademark of L. Perrigo Company

Principal Display Panel

GOODSENSE

SUNSCREEN

CONTINUOUS

SPRAY

BROAD SPECTRUM

SPF 50

Water Resistant

(80 Minutes)

UVA/UVB Protection
Spray at Any Angle
Oxybenzone Free

*Compare and Save 100% Satisfaction Guaranteed

NET WT 5.5 OZ (155 g)